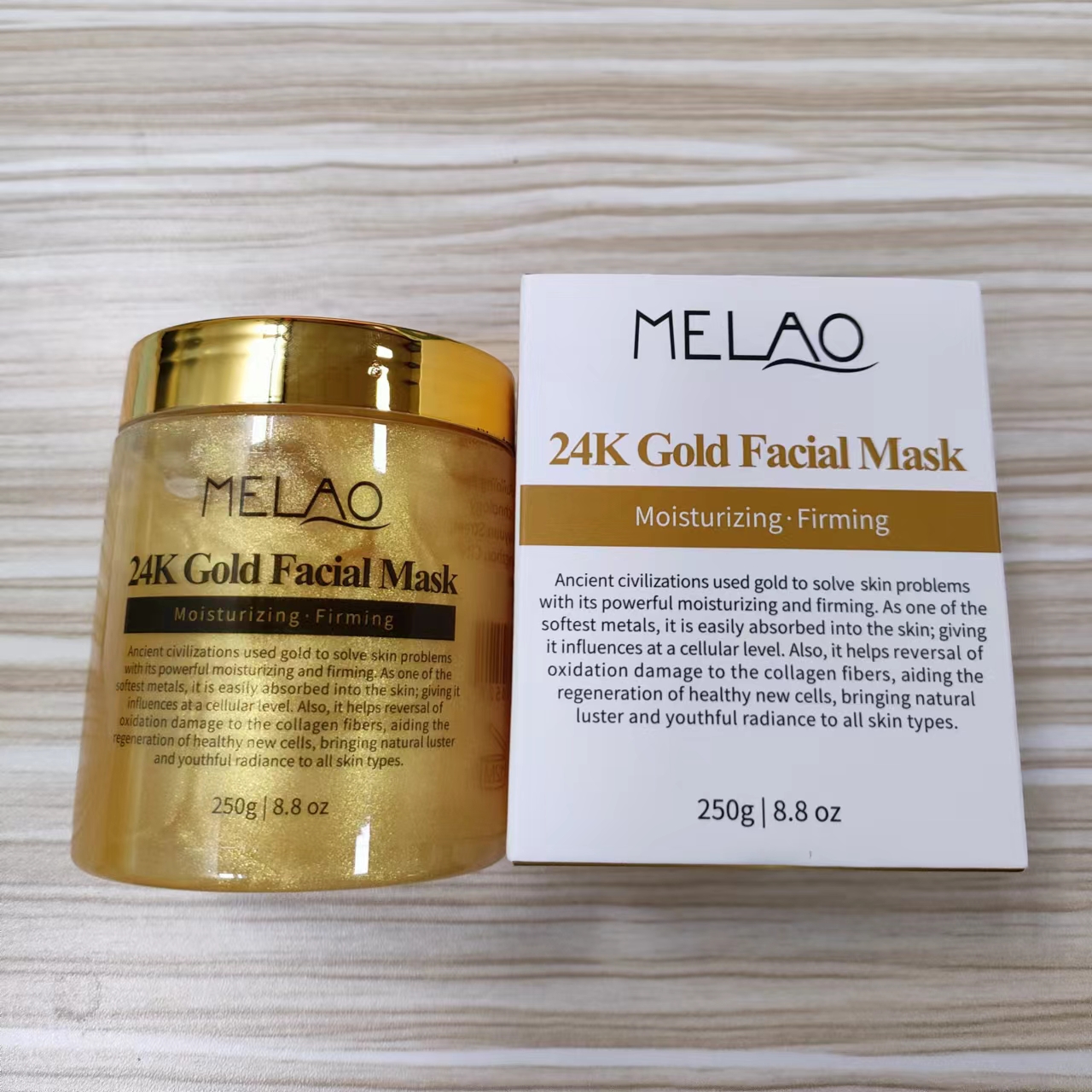 DRUG LABEL: MELAO 24K Gold Facial Mask
NDC: 74458-004 | Form: CREAM
Manufacturer: Guangzhou Yilong Cosmetics Co., Ltd
Category: otc | Type: HUMAN OTC DRUG LABEL
Date: 20241102

ACTIVE INGREDIENTS: SILK AMINO ACIDS 5 g/100 g; ALLANTOIN 0.2 g/100 g; POLYGLUTAMIC ACID (1200 MW) 1 g/100 g
INACTIVE INGREDIENTS: LEONTOPODIUM ALPINUM; CENTELLA ASIATICA; PORTULACA OLERACEA LEAF; GOLD; TOCOPHEROL; SELENICEREUS GRANDIFLORUS FLOWER; XANTHAN GUM; WATER; CODIUM TOMENTOSUM EXTRACT; SODIUM HYALURONATE; BUTYL GLYCOLATE; ARNICA MONTANA FLOWER

MELAO 24K Gold Facial Mask

ACTIVE INGREDIENT

Silk Amino Acids

Polyglutamic Acid

Allantoin

INACTIVE INGREDIENT

Water

Butyl Glycolate

Codium Tomentosum Extracts

Hydrolyzed Collagen

Leontopodium Alpinum Extract

Centella Asiatica Extract

Portulaca Oleracea Extract

Cereus Grandiflorus (Cactus) Extract

Arnica Montana Flower Extract

Sodium Hyaluronate

Tocopherol/Wheat Polypeptides

Xanthan Gum

Gold

INDICATIONS AND USAGE

Using fingertips or brush, gently opply a thin layer directly to the whole face (avoiding eye area),ensuring good contact with the skin。Massage in upward circular motion to your face and relax for~30-45 minutes, and then rinse thoroughly with water.

PURPOSE

Moisturizes and firms skin.

WARNINGS

For external use only.

Stop use and ask a doctor if rash occurs.

Do not use on damaged or broken skin.

When using this product keep out of eyes. Rinse with water to remove.

Keep out of reach of children. If swallowed, get medical help or contact a Poison Control Center right away.

DOSAGE AND ADMINISTRATION

Using fingertips or brush, gently opply a thin layer directly to the whole face (avoiding eye area),ensuring good contact with the skin。Massage in upward circular motion to your face and relax for~30-45 minutes, and then rinse thoroughly with water.